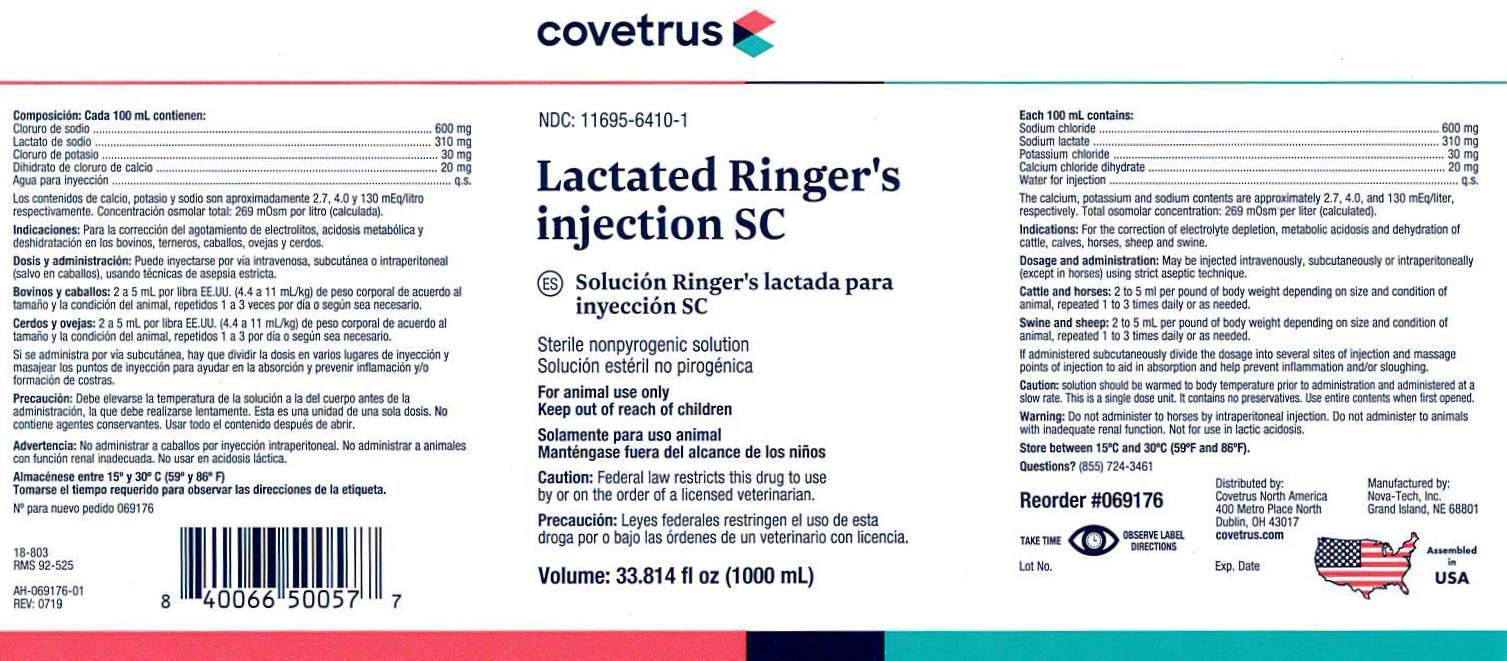 DRUG LABEL: Lactated Ringers
NDC: 11695-6410 | Form: INJECTION, SOLUTION
Manufacturer: Covetrus
Category: animal | Type: PRESCRIPTION ANIMAL DRUG LABEL
Date: 20240424

ACTIVE INGREDIENTS: SODIUM CHLORIDE 600 mg/100 mL; SODIUM LACTATE 310 mg/100 mL; POTASSIUM CHLORIDE 30 mg/100 mL; CALCIUM CHLORIDE 20 mg/100 mL

Lactated Ringers Injection SC

Each 100 mL contains:

Sodium chloride ............................ 600 mg
Sodium lactate .............................. 310 mg
Potassium chloride .......................... 30 mg
Calcium chloride dihydrate ............... 20 mg
Water for injection .............................. q.s.

The calcium, potassium and sodium contents are approximately 2.7, 4.0, and 130 mEq/liter,
respectively. Total osomolar concentration: 269 mOsm per liter (calculated).

INDICATIONS:

For the correction of electrolyte depletion, metabolic acidosis and dehydration
of cattle, calves, horses, sheep and swine.

DOSAGE AND ADMINISTRATION:

May be injected intravenously, subcutaneously or
intraperitoneally (except in horses) using strict aseptic technique.

Cattleand Horses: 2 to 5 mL per pound of body weight depending on size and condition
of animal, repeated 1 to 3 times daily or as needed.

Swineand Sheep: 2 to 5 mL per pound of body weight depending on size and condition
of animal, repeated 1 to 3 times daily or as needed.

If administered subcutaneously divide the dosage into several sites of injection and
massage points of injection to aid in absorption and help prevent inflammation and/or sloughing.

CAUTION:

Solution should be warmed to body temperature prior to administration and
administered at a slow rate. This is a single dose unit. It contains no preservatives. Use entire
contents when first opened.

WARNING:

Do not administer to horses by intraperitoneal injection. Do not administer to
animals with inadequate renal function. Not for use in lactic acidosis.

STORAGE AND HANDLING

Store between 15°C and 30°C (59°F and 86°F)

PRECAUTIONS

TAKE TIME OBSERVE LABEL DIRECTIONS

VETERINARY INDICATIONS

STERILE NONPYROGENIC SOLUTION

FOR ANIMAL USE ONLY

CAUTION:

Federal law restricts this drug to use
by or on the order of a licensed veterinarian.

KEEP OUT OF REACH OF CHILDREN

INFORMATION FOR OWNERS/CAREGIVERS

NDC: 11695-6410-1

Volume: 33.814 fl oz (1000 mL)

Questions? (855) 724-3461

Reorder #069176

Manufactured by
Nova-Tech, Inc.
Grand Island, NE 68801

Distributed by:
Covetrus North America

400 Metro Place North

Dublin, OH 43017
covetrus.com

Lot No. Exp. Date

AH-069176-01
Rev: 0719

18-803
RMS 92-525

Assembled in USA